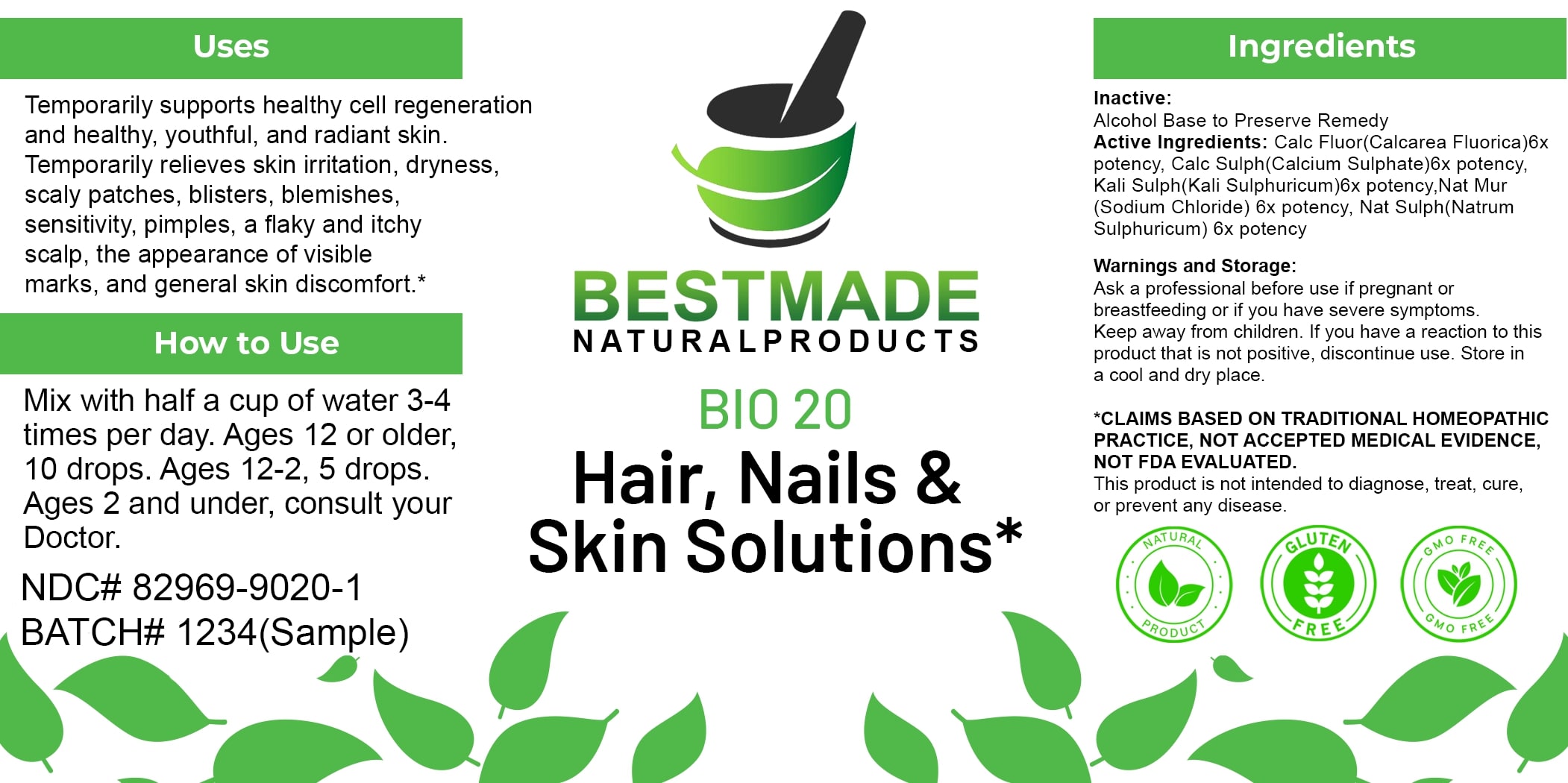 DRUG LABEL: Bestmade Natural Products BIO20
NDC: 82969-9020 | Form: LIQUID
Manufacturer: Bestmade Natural Products
Category: homeopathic | Type: HUMAN OTC DRUG LABEL
Date: 20250311

ACTIVE INGREDIENTS: POTASSIUM SULFATE 6 [hp_X]/6 [hp_X]; SODIUM SULFATE 6 [hp_X]/6 [hp_X]; CALCIUM FLUORIDE 6 [hp_X]/6 [hp_X]; CALCIUM SULFATE ANHYDROUS 6 [hp_X]/6 [hp_X]; SODIUM CHLORIDE 6 [hp_X]/6 [hp_X]
INACTIVE INGREDIENTS: ALCOHOL 6 [hp_X]/6 [hp_X]

BIO 20 Hair, Nails & Skin Solutions*

DOSAGE AND ADMINISTRATION

How to Use

Mix with half a cup of water 3-4 times per day. Ages 12 or older, 10 drops. Ages 12-2, 5 drops. Ages 2 and under, consult your Doctor.

INACTIVE INGREDIENT

Ingredients

Inactive: Alcohol Base to Preserve Remedy

Active Ingredients:

Calc Fluor (Calcarea Fluorica)6x potency, Calc Sulph (Calcium Sulphate) 6x potency, Kali Sulph(Kali Sulphuricum)6x potency, Nat Mur (Sodium Chloride) 6x potency, Nat Sulph (Natrum Sulphuricum) 6x potency

Uses

Temporarily supports healthy cell regeneration and healthy, youthful, and radiant skin. Temporarily relieves skin irritation, dryness, scaly patches, blisters, blemishes, sensitivity, pimples, a flaky and itchy scalp, the appearance of visible marks, and general skin discomfort.*

*CLAIMS BASED ON TRADITIONAL HOMEOPATHIC PRACTICE, NOT ACCEPTED MEDICAL EVIDENCE. NOT FDA EVALUATED.

This product is not intended to diagnose, treat, cure, or prevent any disease.

Uses

Temporarily supports healthy cell regeneration and healthy, youthful, and radiant skin. Temporarily relieves skin irritation, dryness, scaly patches, blisters, blemishes, sensitivity, pimples, a flaky and itchy scalp, the appearance of visible marks, and general skin discomfort.*

*CLAIMS BASED ON TRADITIONAL HOMEOPATHIC PRACTICE, NOT ACCEPTED MEDICAL EVIDENCE. NOT FDA EVALUATED.

This product is not intended to diagnose, treat, cure, or prevent any disease.

KEEP OUT OF REACH OF CHILDREN

Warnings and Storage:

Ask a professional before use if pregnant or breastfeeding or if you have severe symptoms. Keep away from children. If you have a reaction to this product that is not positive, discontinue use. Store in a cool and dry place.

Warnings and Storage:

Ask a professional before use if pregnant or breastfeeding or if you have severe symptoms. Keep away from children. If you have a reaction to this product that is not positive, discontinue use. Store in a cool and dry place.

*CLAIMS BASED ON TRADITIONAL HOMEOPATHIC PRACTICE, NOT ACCEPTED MEDICAL EVIDENCE NOT FDA EVALUATED.

This product is not intended to diagnose, treat, cure, or prevent any disease.

Entire package label